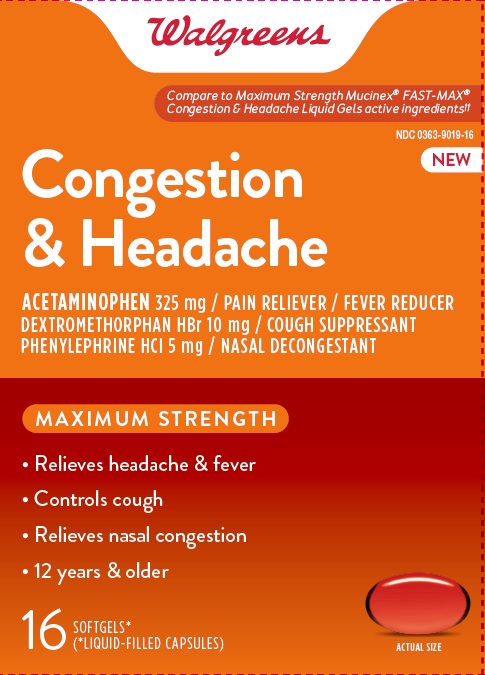 DRUG LABEL: Maximum Strength Congestion and Headache
NDC: 0363-9019 | Form: CAPSULE, LIQUID FILLED
Manufacturer: Walgreens
Category: otc | Type: HUMAN OTC DRUG LABEL
Date: 20260116

ACTIVE INGREDIENTS: ACETAMINOPHEN 325 mg/1 1; DEXTROMETHORPHAN HYDROBROMIDE 10 mg/1 1; PHENYLEPHRINE HYDROCHLORIDE 5 mg/1 1
INACTIVE INGREDIENTS: FD&C RED NO. 40; FD&C YELLOW NO. 6; GELATIN; GLYCERIN; POLYETHYLENE GLYCOL 400; POVIDONE K30; PROPYLENE GLYCOL; SORBITOL; SORBITAN; TITANIUM DIOXIDE; WATER

Walgreens Maximum Strength Congestion & Headache

Drug Facts

ACTIVE INGREDIENT

PURPOSE

Active ingredients (in each liquid gel) | Purposes
Acetaminophen 325 mg | Pain reliever/fever reducer
Dextromethorphan HBr 10 mg | Cough suppressant
Phenylephrine HCl 5 mg | Nasal decongestant

Uses

- temporarily relieves these common cold and flu symptoms:
  - nasal congestion
  - cough
  - headache
  - minor aches and pains
  - sinus congestion and pressure
- temporarily reduces fever
- temporarily promotes nasal and/or sinus drainage

Warnings

Liver warning

This product contains acetaminophen. Severe liver damage may occur if you take:

- more than 12 softgels in 24 hours, which is the maximum daily amount
- with other drugs containing acetaminophen
- 3 or more alcoholic drinks daily while using this product

Allergy alert

Acetaminophen may cause severe skin reactions. Symptoms may include:

- skin reddening
- blisters
- rash

If a skin reaction occurs, stop use and seek medical help right away.

Do not use

- with any other drug containing acetaminophen (prescription or nonprescription). If you are not sure whether a drug contains acetaminophen, ask a doctor or pharmacist.
- if you are now taking a prescription monoamine oxidase inhibitor (MAOI) (certain drugs for depression, psychiatric, or emotional conditions, or Parkinson's disease), or for 2 weeks after stopping the MAOI drug. If you do not know if your prescription drug contains an MAOI, ask a doctor or pharmacist before taking this product.

Ask a doctor before use if you have

- liver disease
- heart disease
- diabetes
- high blood pressure
- thyroid disease
- trouble urinating due to an enlarged prostate gland
- persistent or chronic cough such as occurs with smoking, asthma, or emphysema
- cough that occurs with too much phlegm (mucus)

Ask a doctor or pharmacist before use if you are taking the blood thinning drug warfarin

When using this product do not use more than directed

Stop use and ask a doctor if

- nervousness, dizziness, or sleeplessness occur
- pain, nasal congestion, or cough gets worse or lasts more than 7 days
- fever gets worse or lasts more than 3 days
- redness or swelling is present
- new symptoms occur
- cough comes back, or occurs with rash or headache that lasts. These could be signs of a serious condition.

PREGNANCY OR BREAST FEEDING

If pregnant or breast-feeding, ask a health professional before use.

Keep out of reach of children.

Overdose warning

Taking more than the recommended dose (overdose) may cause liver damage. In case of overdose, get medical help or contact a Poison Control Center right away. Quick medical attention is critical for adults as well as for children even if you do not notice any signs or symptoms.

Directions

- do not take more than directed (see Overdose warning)
- do not take more than 12 softgels in any 24-hour period
- adults and children 12 years of age and older: take 2 softgels every 4 hours
- children under 12 years of age: do not use

Other information

- store at 20-25°C (68-77°F)
- avoid excessive heat

Inactive ingredients

FD&C Red# 40, FD&C Yellow#
6, gelatin, glycerin, polyethylene glycol, povidone,
propylene glycol, purified water, sorbitol sorbitan, titanium
dioxide

Questions or comments?

1-888-333-9792

PRINCIPAL DISPLAY PANEL

MAXIMUM STRENGTH

CONGESTION &
HEADACHE

Acetaminophen – Pain Reliever/Fever Reducer
Dextromethorphan HBr – Cough Suppressant
Phenylephrine HCl – Nasal Decongestant

Relieves Headache & Fever
Controls Cough
Relieves Nasal Congestion
16
SOFTGELS